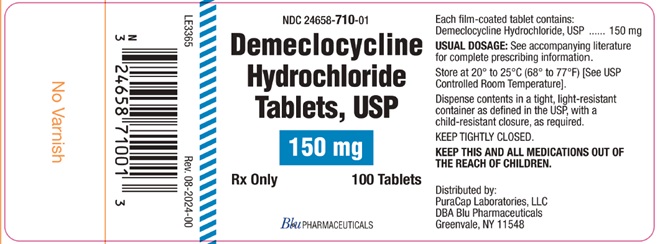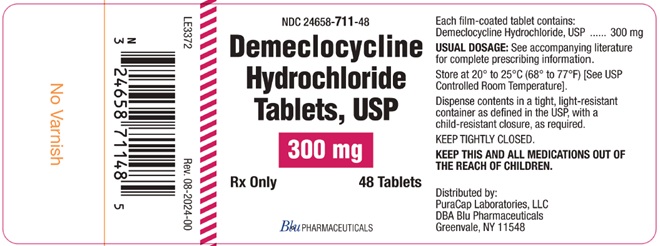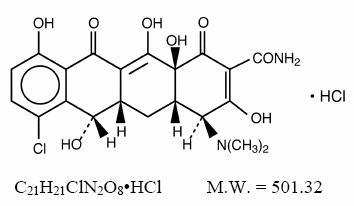 DRUG LABEL: Demeclocycline Hydrochloride
NDC: 24658-710 | Form: TABLET, FILM COATED
Manufacturer: PuraCap Laboratories LLC
Category: prescription | Type: HUMAN PRESCRIPTION DRUG LABEL
Date: 20251211

ACTIVE INGREDIENTS: DEMECLOCYCLINE HYDROCHLORIDE 150 mg/1 1
INACTIVE INGREDIENTS: SILICON DIOXIDE; CARNAUBA WAX; MAGNESIUM STEARATE; HYPROMELLOSE 2910 (10000 MPA.S); FD&C YELLOW NO. 6; D&C RED NO. 30; D&C RED NO. 27; FD&C BLUE NO. 1; FD&C RED NO. 40; POLYETHYLENE GLYCOL 8000; TITANIUM DIOXIDE; TRIACETIN; STARCH, CORN; TALC; POLYDEXTROSE; CROSPOVIDONE (120 .MU.M); MICROCRYSTALLINE CELLULOSE; HYDROXYPROPYL CELLULOSE (90000 WAMW)

Demeclocycline Hydrochloride Tablets
Rx Only

Full Prescribing Information

To reduce the development of drug-resistant bacteria and maintain the effectiveness of demeclocycline hydrochloride tablets and other antibacterial drugs, demeclocycline hydrochloride tablets should be used only to treat or prevent infections that are proven or strongly suspected to be caused by bacteria.

DESCRIPTION

Demeclocycline hydrochloride, USP is an antibiotic isolated from a mutant strain of Streptomyces aureofaciens. Chemically it is 7- Chloro-4-(dimethylamino)-1,4,4a,5,5a,6,11,12a-octahydro-3,6,10,12, 12a-pentahydroxy-1,11-dioxo-2-naphthacenecarboxamide monohydrochloride.

Its structural formula is:

Each film-coated tablet for oral administration contains 150 mg or 300 mg of demeclocycline hydrochloride, USP and has the following inactive ingredients: carnauba wax, colloidal silicon dioxide, crospovidone, hydroxypropyl cellulose, hypromelloses, magnesium stearate, microcrystalline cellulose, polydextrose, polyethylene glycol, pregelatinized starch, talc, titanium dioxide, triacetin, D&C Red No. 27 Aluminum Lake, D&C Red No. 30 Aluminum Lake, FD&C Blue No. 1 Aluminum Lake and FD&C Yellow No. 6 Aluminum Lake.

CLINICAL PHARMACOLOGY

Pharmacokinetics

The absorption of demeclocycline is slower than that of tetracycline. The time to reach the peak concentration is about 4 hours. After a 150 mg oral dose of demeclocycline tablet, the mean concentrations at 1 hour and 3 hours are 0.46 and 1.22 mcg/mL (n = 6), respectively. The serum half-life ranges between 10 and 16 hours. When demeclocycline hydrochloride is given concomitantly with some dairy products, or antacids containing aluminum, calcium, or magnesium, the extent of absorption is reduced by more than 50%. Demeclocycline hydrochloride penetrates well into various body fluids and tissues. The percent of demeclocycline hydrochloride bound to plasma protein is about 40% using a dialysis equilibrium method and 90% using an ultra-filtration method. Demeclocycline hydrochloride, like other tetracyclines, is concentrated in the liver and excreted into the bile where it is found in much higher concentrations than in the blood. The rate of demeclocycline hydrochloride renal clearance (35 mL/min/1.73 m^2) is less than half that of tetracycline. Following a single 150 mg dose of demeclocycline hydrochloride in normal volunteers, 44% (n = 8) was excreted in urine and 13% and 46%, respectively, were excreted in feces in two patients within 96 hours as active drug.

Microbiology

Mechanism of Action

The tetracyclines are primarily bacteriostatic and are thought to exert their antimicrobial effect by the inhibition of protein synthesis. The tetracyclines, including demeclocycline, have a similar antimicrobial spectrum of activity against a wide range of gram-negative and gram-positive organisms.

Mechanism(s) of Resistance

Resistance to tetracyclines may be mediated by efflux, alteration in the target site of tetracycline, enzymatic inactivation, and decreased bacterial permeability to the tetracycline or a combination of these mechanisms.

Cross-Resistance

Cross-resistance between antibiotics of the tetracycline family occurs.

Demeclocycline has been shown to be active against most isolates of the following bacteria, in vitro and/or in clinical infections as described in the INDICATIONS AND USAGE section.

Gram-Positive Bacteria

Bacillus anthracis

Listeria monocytogenes

Staphylococcus aureus

Streptococcus pneumoniae

Gram-Negative Bacteria

Bartonella bacilliformis

Brucella species

Calymmatobacterum granulomatis

Campylobacter fetus

Francisella tularensis

Haemophilus ducreyi

Haemophilus influezae

Neisseria gonorrrhoeae

Vibrio cholerae

Yersinia pestis

Because many isolates of the following groups of gram-negative bacteria have been shown to be resistant to tetracyclines, culture and susceptibility testing are especially recommended:

Acinetobacter species

Enterobacter aerogenes

Escherichia coli

Klebsiella species

Shigella species

Other Microorganisms

Actinomyces israelii

Borella recurrentis

Chlamydia psittaci

Chlamydia trachomatis

Clostridium species

Entamoeba species

Fusobacterium fusiforme

Mycoplasma pneumoniae

Propionibacterium acnes

Rickettsiae

Treponema pallidium subspecies pallidum

Treponema pallidum subspecies pertenue

Ureaplasma urealyticum

Susceptibility Test Methods

When available, the clinical microbiology laboratory should provide the results of in vitro susceptibility test results for antimicrobial drug products used in resident hospitals to the physician as periodic reports that describe the susceptibility profile of nosocomial and community-acquired pathogens. These reports should aid the physician in selecting an antibacterial drug product for treatment

Dilution Techniques

Quantitative methods are used to determine antimicrobial minimum inhibitory concentrations (MICs). These MICs provide estimates of the susceptibility of bacteria to antimicrobial compounds. The MICs should be determined using a standardized method (broth/or agar)^1,2,3. The MIC values should be interpreted according to the criteria in Table 1.

Diffusion Techniques

Quantitative methods that require measurement of zone diameters can also provide reproducible estimates of the susceptibility of bacteria to antimicrobial compounds. The zone size provides an estimate of the susceptibility of bacteria to antimicrobial compounds.

The zone size should be determined using a standardized test method.^2,4 This procedure uses paper disks impregnated with 30 mcg tetracycline to test the susceptibility of microorganisms to tetracycline. The disc diffusion interpretive criteria are provided in Table 1.

Table 1. Susceptibility Test Interpretive Criteria for Tetracycline
 | Minimum Inhibitory Concentration; (mcg/mL) |  |  | Disk Diffusion; (zone diameters in mm)
Pathogen
 | S | I | R | S | I | R
Enerobacteriaceae, Acinetobacter spp. | ≤4 | 8 | >16 | ≥15 | 12 to 14 | <11
Haemophilus influenzae | <2 | 4 | >8 | >29 | 26 to 28 | <25
Neisseria gonorrhoeae | <0.25 | 0.5 to 1 | >2 | >38 | 31 to 37 | <30
Staphylococcus aureus | ≤4 | 8 | ≥16 | ≥19 | 15 to 18 | ≤14
S. pneumoniae (non-meningitis isolates) | ≤1 | 2 | ≥4 | >28 | 25 to 27 | ≤24
Bacillus anthracis | <1 | -- | -- | -- | -- | --
Francisella tularensis | <4 | -- | -- | -- | -- | --

A report of Susceptible indicates that the antimicrobial is likely to inhibit growth of the pathogen if the antimicrobial compound reaches the concentrations at the infection site necessary to inhibit growth of the pathogen. A report of Intermediate indicates that the result should be considered equivocal, and, if the microorganism is not fully susceptible to alternative, clinically feasible drugs, the test should be repeated. This category implies possible clinical applicability in body sites where the drug product is physiologically concentrated or in situations where a high dosage of the drug product can be used. This category also provides a buffer zone that prevents small uncontrolled technical factors from causing major discrepancies in interpretation. A report of Resistant indicates that the antimicrobial is not likely to inhibit growth of the pathogen if the antimicrobial compound reaches the concentrations usually achievable at the infection site; other therapy should be selected.

Quality Control

Standardized susceptibility test procedures require the use of laboratory controls to monitor and ensure the accuracy and precision of supplies and reagents used in the assay, and the techniques of the individuals performing the test.^1,2,3,4 Standard tetracycline powder should provide the following range of MIC values noted in Table 2. For the diffusion technique using the 30 mcg tetracycline disk, the criteria in Table 2 should be achieved.

Table 2. Acceptable Quality Control Ranges for Tetracycline
QC Strain | Minimum Inhibitory Concentrations (mcg/mL) | Disk Diffusion (zone diameters in mm)
Escherichia coli ATCC* 25922 | 0.5 to 2 | 18 to 25
Staphylococcus aureus ATCC 29213 | 0.12 to 1 | -----
Staphylococcus aureus ATCC 25923 | ----- | 24 to 30
Haemophilus influenzae ATCC 49247 | 4 to 32 | 14 to 22
Neisseria gonorrhoeae ATCC 49226 | 0.25 to 1 | 30 to 42
Streptococcus pneumoniae ATCC 49619 | 0.06 to 0.5 | 27 to 31
*ATCC = American Type Culture Collection

INDICATIONS AND USAGE

Demeclocycline hydrochloride tablets USP is indicated in the treatment of infections caused by susceptible strains of the designated microorganisms in the conditions below:

Rocky Mountain spotted fever, typhus fever and the typhus group, Q fever, rickettsialpox, and tick fevers caused by rickettsiae; Respiratory tract infections caused by Mycoplasma pneumoniae; Lymphogranuloma venereum due to Chlamydia trachomatis; Psittacosis (Ornithosis) due to Chlamydia psittaci; Trachoma due to Chlamydia trachomatis, although the infectious agent is not always eliminated, as judged by immunofluorescence; Inclusion conjunctivitis caused by Chlamydia trachomatis; Nongonococcal urethritis in adults caused by Ureaplasma urealyticum or Chlamydia trachomatis; Relapsing fever due to Borrelia recurrentis;
Chancroid caused by Haemophilus ducreyi;

Plague due to Yersinia pestis;

Tularemia due to Francisella tularensis;

Cholera caused by Vibrio cholerae;

Campylobacter fetus infections caused by Campylobacter fetus;

Brucellosis due to Brucella species (in conjunction with streptomycin);

Bartonellosis due to Bartonella bacilliformis;

Granuloma inguinale caused by Calymmatobacterium granulomatis;

Demeclocycline hydrochloride tablets USP is indicated for treatment of infections caused by the following gram-negative microorganisms, when bacteriologic testing indicates appropriate susceptibility to the drug:

Escherichia coli;

Enterobacter aerogenes;

Shigella species;

Acinetobacter species;

Respiratory tract infections caused by Haemophilus influenzae;

Respiratory tract and urinary tract infections caused by Klebsiella species.

Demeclocycline hydrochloride tablets USP is indicated for treatment of infections caused by the following gram-positive microorganisms, when bacteriologic testing indicates appropriate susceptibility to the drug:

Upper respiratory infections caused by Streptococcus pneumoniae;

Skin and skin structure infections caused by Staphylococcus aureus.

(Note: Tetracyclines, including demeclocycline, are not the drugs of choice in the treatment of any type of staphylococcal infection.) When penicillin is contraindicated, tetracyclines, including demeclocycline hydrochloride, are alternative drugs in the treatment of the following infections:

Uncomplicated urethritis in men due to Neisseria gonorrhoeae, and for the treatment of other uncomplicated gonococcal infections; Infections in women caused by Neisseria gonorrhoeae;

Syphilis caused by Treponema pallidum subspecies pallidum;

Yaws caused by Treponema pallidum subspecies pertenue;

Listeriosis due to Listeria monocytogenes;

Anthrax due to Bacillus anthracis;

Vincent’s infection caused by Fusobacterium fusiforme;

Actinomycosis caused by Actinomyces israelii;

Clostridial diseases caused by Clostridium species.

In acute intestinal amebiasis, demeclocycline hydrochloride tablets USP may be a useful adjunct to amebicides.

In severe acne, demeclocycline hydrochloride tablets USP may be a useful adjunctive therapy.

To reduce the development of drug-resistant bacteria and maintain the effectiveness of demeclocycline hydrochloride tablets USP and other antibacterial drugs, demeclocycline hydrochloride tablets USP should be used only to treat or prevent infections that are proven or strongly suspected to be caused by susceptible bacteria. When culture and susceptibility information are available, they should be considered in selecting or modifying antibacterial therapy. In the absence of such data, local epidemiology and susceptibility patterns may contribute to the empiric selection of therapy.

CONTRAINDICATIONS

This drug is contraindicated in persons who have shown hypersensitivity to any of the tetracyclines or any of the components of the product formulation.

WARNINGS

DEMECLOCYCLINE HYDROCHLORIDE, LIKE OTHER TETRACYCLINE-CLASS ANTIBIOTICS, CAN CAUSE FETAL HARM WHEN ADMINISTERED TO A PREGNANT WOMAN. IF ANY TETRACYCLINE IS USED DURING PREGNANCY, OR IF THE PATIENT BECOMES PREGNANT WHILE TAKING THESE DRUGS, THE PATIENT SHOULD BE APPRISED OF THE POTENTIAL HAZARD TO THE FETUS.

THE USE OF DRUGS OF THE TETRACYCLINE CLASS DURING TOOTH DEVELOPMENT (LAST HALF OF PREGNANCY, INFANCY AND CHILDHOOD TO THE AGE OF 8 YEARS) MAY CAUSE PERMANENT DISCOLORATION OF THE TEETH (YELLOW-GRAY-BROWN). This adverse reaction is more common during long-term use of the drugs but has been observed following repeated short-term courses. Enamel hypoplasia has also been reported. TETRACYCLINE DRUGS, THEREFORE, SHOULD NOT BE USED DURING TOOTH DEVELOPMENT UNLESS OTHER DRUGS ARE NOT LIKELY TO BE EFFECTIVE OR ARE CONTRAINDICATED.

All tetracyclines form a stable calcium complex in any bone-forming tissue. A decrease in fibula growth rate has been observed in premature human infants given oral tetracycline in doses of 25 mg/kg every six hours. This reaction was shown to be reversible when the drug was discontinued.

Results of animal studies indicate that tetracyclines cross the placenta, are found in fetal tissues, and can have toxic effects on the developing fetus (often related to retardation of skeletal development). Evidence of embryotoxicity has also been noted in animals treated early in pregnancy. The anti-anabolic action of the tetracyclines may cause an increase in BUN. While this is not a problem in those with normal renal function, in patients with significantly impaired function, higher serum levels of tetracycline may lead to azotemia, hyperphosphatemia, and acidosis.

If renal impairment exists, even usual oral or parenteral doses may lead to excessive systemic accumulation of the drug and possible liver toxicity. Under such conditions, lower than usual total doses are indicated and, if therapy is prolonged, serum level determinations of the drug may be advisable.

Photosensitivity manifested by an exaggerated sunburn reaction has been observed in some individuals taking tetracyclines. Phototoxic reactions can occur in individuals taking demeclocycline, and are characterized by severe burns or exposed surfaces resulting from direct exposure of patients to sunlight during therapy with moderate or large doses of demeclocycline. Patients apt to be exposed to direct sunlight or ultraviolet light should be advised that this reaction can occur, and treatment should be discontinued at the first evidence of erythema of the skin.

Administration of demeclocycline hydrochloride has resulted in appearance of the diabetes insipidus syndrome (polyuria, polydipsia and weakness) in some patients on long-term therapy. The syndrome has been shown to be nephrogenic, dose-dependent and reversible on discontinuance of therapy. Patients who are experiencing central nervous system symptoms associated with demeclocycline therapy should be cautioned about driving vehicles or using hazardous machinery while on demeclocycline therapy. Clostridium difficile associated with diarrhea (CDAD) has been reported with use of nearly all antibacterial agents, including demeclocycline hydrochloride, and may range in severity from mild diarrhea to fatal colitis. Treatment with antibacterial agents alters the normal flora of the colon leading to overgrowth of C. difficile.

C. difficile produces toxins A and B which contribute to the development of CDAD. Hypertoxin producing strains of C. difficile cause increased morbidity and mortality, as these infections can be refractory to antimicrobial therapy and may require colectomy. CDAD must be considered in all patients who present with diarrhea following antibiotic use. Careful medical history is necessary since CDAD has been reported to occur over two months after the administration of antibacterial agents.

If CDAD is suspected or confirmed, ongoing antibiotic use not directed against C. difficile may need to be discontinued. Appropriate fluid and electrolyte management, protein supplementation, antibiotic treatment of C. difficile, and surgical evaluation should be instituted as clinically indicated.

PRECAUTIONS

General

Pseudotumor cerebri (benign intracranial hypertension) in adults has been associated with the use of tetracyclines. The usual clinical manifestations are headache and blurred vision. Bulging fontanels have been associated with the use of tetracyclines in infants. While both of these conditions and related symptoms usually resolve soon after discontinuation of the tetracycline, the possibility for permanent sequelae exists.

As with other antibiotic preparations, use of this drug may result in overgrowth of nonsusceptible organisms, including fungi. If superinfection occurs, the antibiotic should be discontinued and appropriate therapy should be instituted.

Incision and drainage or other surgical procedures should be performed in conjunction with antibiotic therapy, when indicated.

Prescribing demeclocycline hydrochloride tablets in the absence of a proven or strongly suspected bacterial infection or a prophylactic indication is unlikely to provide benefit to the patient and increases the risk of the development of drug-resistant bacteria.

Information for Patients

Photosensitivity manifested by an exaggerated sunburn reaction has been observed in some individuals taking tetracyclines. Patients apt to be exposed to direct sunlight or ultraviolet light should be advised that this reaction can occur with tetracycline drugs, and treatment should be discontinued at the first evidence of skin erythema. Concurrent use of tetracyclines with oral contraceptives may render oral contraceptives less effective (see Drug Interactions). Patients should be informed that demeclocycline hydrochloride tablets should be taken at least 1 hour before meals or 2 hours after meals (see DOSAGE AND ADMINISTRATION). Unused supplies of tetracycline antibiotics should be discarded by the expiration date. Patients who are experiencing headache, dizziness, light-headedness, vertigo, or blurred vision while on demeclocycline therapy, should be cautioned about driving vehicles or using hazardous machinery while receiving demeclocycline therapy (see WARNINGS).

Patients should be counseled that antibacterial drugs, including demeclocycline hydrochloride tablets should only be used to treat bacterial infections. They do not treat viral infections (e.g., the common cold). When demeclocycline hydrochloride tablets are prescribed to treat a bacterial infection, patients should be told that although it is common to feel better early in the course of therapy, the medication should be taken exactly as directed.

Skipping doses or not completing the full course of therapy may (1) decrease the effectiveness of the immediate treatment and (2) increase the likelihood that bacteria will develop resistance and will not be treatable by demeclocycline hydrochloride tablets or other antibacterial drugs in the future.

Diarrhea is a common problem caused by antibiotics which usually ends when the antibiotic is discontinued. Sometimes after starting treatment with antibiotics, patients can develop watery and bloody stools (with or without stomach cramps and fever) even as late as two or more months after having taken the last dose of the antibiotic. If this occurs, patients should contact their physician as soon as possible.

Laboratory Tests

In venereal diseases when coexistent syphilis is suspected, darkfield examination should be done before treatment is started and the blood serology repeated monthly for at least 4 months. In long-term therapy, periodic laboratory evaluation of organ systems, including hematopoietic, renal, and hepatic, should be performed. All patients with gonorrhea should have a serologic test for syphilis at the time of diagnosis. Patients treated with demeclocycline hydrochloride should have a follow-up serologic test for syphilis after 3 months.

Drug Interactions

Because tetracyclines have been shown to depress plasma prothrombin activity, patients who are on anticoagulant therapy may require downward adjustment of their anticoagulant dosage. Since bacteriostatic drugs may interfere with the bactericidal action of penicillins, it is advisable to avoid giving tetracycline-class drugs in conjunction with penicillin.

Concurrent use of tetracyclines with oral contraceptives may render oral contraceptives less effective.

The concurrent use of tetracyclines and methoxyflurane has been reported to result in fatal renal toxicity.

Absorption of tetracyclines is impaired by antacids containing aluminum, calcium or magnesium, and by iron-containing preparations.

Carcinogenesis, Mutagenesis, Impairment of Fertility

Long-term studies in animals to evaluate carcinogenic potential of demeclocycline hydrochloride have not been conducted. However, there has been evidence of oncogenic activity in rats in studies with the related antibiotics oxytetracycline (adrenal and pituitary tumors) and minocycline (thyroid tumors).

Although mutagenicity studies of demeclocycline hydrochloride have not been conducted, positive results in in vitro mammalian cell assays (i.e., mouse lymphoma and Chinese hamster lung cells) have been reported for related antibiotics (tetracycline hydrochloride and oxytetracycline). (See WARNINGS; ANIMAL PHARMACOLOGY AND ANIMAL TOXICOLOGY.)

Demeclocycline hydrochloride had no effect on fertility when administered in the diet to male and female rats at a daily intake of 45 times the human dose.

Pregnancy

Teratogenic Effects

Pregnancy Category D

(See WARNINGS).

Results of animal studies indicate that tetracyclines cross the placenta, are found in fetal tissues, and can have toxic effects on the developing fetus (often related to retardation of skeletal development). Evidence of embryotoxicity has been noted in animals treated early in pregnancy.

Nonteratogenic Effects

(See WARNINGS).

Labor and Delivery

The effect of tetracyclines on labor and delivery is unknown.

Nursing Mothers

Tetracyclines are excreted in human milk. Because of the potential for serious adverse reactions in nursing infants from the tetracyclines, a decision should be made whether to discontinue nursing or discontinue the drug, taking into account the importance of the drug to the mother. (See WARNINGS).

Pediatric Use

Not for use in patients younger than eight years of age. (See WARNINGS, PRECAUTIONS, General and DOSAGE AND ADMINISTRATION.)

ADVERSE REACTIONS

The following reactions have been reported in patients receiving tetracyclines:

Gastrointestinal: Anorexia, nausea, vomiting, diarrhea, glossitis, dysphagia, enterocolitis, pancreatitis, and inflammatory lesions (with monilial overgrowth) in the anogenital region, increases in liver enzymes, and hepatic toxicity have been reported rarely.

Rarely, hepatitis and liver failure have been reported. These reactions have been caused by both the oral and parenteral administration of tetracyclines.

Instances of esophageal ulcerations have been reported in patients receiving oral tetracyclines. Most of the patients were reported to have taken the medication immediately before lying down. (See DOSAGE AND ADMINISTRATION)

Skin: Maculopapular and erythematous rashes, erythema multiforme. Exfoliative dermatitis has been reported but is uncommon. Fixed drug eruptions and Stevens-Johnson syndrome have been reported rarely. Lesions occurring on the glans penis have caused balanitis. Pigmentation of the skin and mucous membranes has also been reported. Photosensitivity is discussed above. (See WARNINGS).

Renal toxicity: Acute renal failure. Rise in BUN has been reported and is apparently dose related. Nephrogenic diabetes insipidus. (See WARNINGS.)

Hypersensitivity reactions: Urticaria, angioneurotic edema, polyarthralgia, anaphylaxis, anaphylactoid purpura, pericarditis, exacerbation of systemic lupus erythematosus, lupus-like syndrome, pulmonary infiltrates with eosinophilia.

Hematologic: Hemolytic anemia, thrombocytopenia, neutropenia and eosinophilia have been reported.

CNS: Pseudotumor cerebri (benign intracranial hypertension) in adults and bulging fontanels in infants (see PRECAUTIONS, General). Dizziness, headache, tinnitus, and visual disturbances have been reported. Myasthenic syndrome has been reported rarely.

Other: When given over prolonged periods, tetracyclines have been reported to produce brown-black microscopic discoloration of thyroid glands. No abnormalities of thyroid function studies are known to occur. Very rare cases of abnormal thyroid function have been reported.

Tooth discoloration has occurred in pediatric patients less than 8 years of age (see WARNINGS), and has been reported rarely in adults.

OVERDOSAGE

In case of overdosage, discontinue medication, treat symptomatically and institute supportive measures. Tetracyclines are not removed in significant quantities by hemodialysis or peritoneal dialysis.

DOSAGE AND ADMINISTRATION

Therapy should be continued for at least 24 to 48 hours after symptoms and fever have subsided.

Concomitant Therapy

Absorption of tetracyclines is impaired by antacids containing aluminum, calcium, or magnesium, and by iron-containing preparations. Foods and some dairy products also interfere with absorption. Oral forms of tetracycline should be given at least 1 hour before or 2 hours after meals.

In Patients With Renal Impairment

(See WARNINGS). Tetracyclines should be used cautiously in patients with impaired renal function. Total dosage should be decreased by reduction of recommended individual doses and/or by extending time intervals between doses.

In Patients With Liver Impairment

Tetracyclines should be used cautiously in patients with impaired liver function. Total dosage should be decreased by reduction of recommended individual doses and/or by extending time intervals between doses. Administration of adequate amounts of fluid with the oral formulations of tetracyclines is recommended to wash down the drugs and reduce the risk of esophageal irritation and ulceration. (See ADVERSE REACTIONS).

HOW SUPPLIED

Adults

Usual Daily Dose

Four divided doses of 150 mg each or two divided doses of 300 mg each.

For Pediatric Patients Above Eight Years of Age

Usual daily dose, 7 to 13 mg per kg body weight per day, depending upon the severity of the disease, divided into two to four doses not to exceed adult dosage of 600 mg per day.

Gonorrhea patients sensitive to penicillin may be treated with demeclocycline administered as an initial oral dose of 600 mg followed by 300 mg every 12 hours for four days to a total of 3 grams.

Demeclocycline Hydrochloride Tablets USP, 150 mg, are red, round, biconvex, film-coated tablets, debossed with "Є" above "143" on one side and plain on the other side.

They are supplied as follows:

NDC 24658-710-01 - Bottle of 100 Tablets

Demeclocycline Hydrochloride Tablets USP, 300 mg, are red, round, biconvex, film-coated tablets, debossed with "Є" above "144" on one side and plain on the other side.

They are supplied as follows:

NDC 24658-711-48 - Bottle of 48 Tablets

Store at 20° to 25°C (68° to 77°F) [See USP Controlled Room Temperature].

Dispense contents in a tight, light-resistant container as defined in the USP, with a child-resistant closure as required.

KEEP THIS AND ALL MEDICATIONS OUT OF THE REACH OF CHILDREN.

ANIMAL PHARMACOLOGY AND ANIMAL TOXICOLOGY

Hyperpigmentation of the thyroid has been produced by members of the tetracycline class in the following species: in rats by oxytetracycline, doxycycline, tetracycline PO4 and methacycline; in minipigs by doxycycline, minocycline, tetracycline PO4, and methacycline; in dogs by doxycycline and minocycline; in monkeys by minocycline.

Minocycline, tetracycline PO4, methacycline, doxycycline, tetracycline base, oxytetracycline HCl, and tetracycline HCl were goitrogenic in rats fed a low iodine diet. This goitrogenic effect was accompanied by high radioactive iodine uptake. Administration of minocycline also produced a large goiter with high radioiodine uptake in rats fed a relatively high iodine diet.

Treatment of various animal species with this class of drugs has also resulted in the induction of thyroid hyperplasia in the following: in rats and dogs (minocycline), in chickens (chlortetracycline), and in rats and mice (oxytetracycline). Adrenal gland hyperplasia has been observed in goats and rats treated with oxytetracycline.

REFERENCES

1. Clinical and Laboratory Standards Institute (CLSI.) Methods for Dilution Antimicrobial Susceptibility Tests for Bacteria that Grow Aerobically. Approved Standard - 9th Edition. CLSI document M7-A9, 950 West Valley Rd. Suite 2500, Wayne, PA 19087, 2012.

2. CLSI. Performance Standards for Antimicrobial Susceptibility Testing. 22nd Informational Supplement. CLSI document M100-S22. Wayne, PA, 2012.

3. CLSI. Methods or Antimicrobial Dilution and Disk Susceptibility Testing of Infrequently Isolated or Fastidious Bacteria: Approved Guideline - 2nd Edition. CLSI document M45-A2, CLSI, Wayne, PA, 2011.

4. CLSI, Performance Standards for Antimicrobial Disk Susceptibility Tests. Approved Standard - 11th Edition. CLSI document M2-A11. Wayne, PA, 2012.

Distributed by:

PuraCap Laboratories, LLC

DBA Blu Pharmaceuticals

Greenvale, NY 11548

Rev. 08-2024-00

MF710REV08/24B

OE2575

PACKAGE/LABEL PRINCIPAL DISPLAY PANEL - 150 mg

Demeclocycline Hydrochloride Tablets, USP

150 mg

Rx Only

100 Tablets

PACKAGE/LABEL PRINCIPAL DISPLAY PANEL - 300 mg

Demeclocycline Hydrochloride Tablets, USP

300 mg

Rx Only

48 Tablets